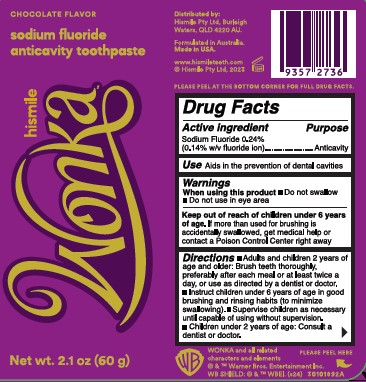 DRUG LABEL: HISMILE
NDC: 44038-0325 | Form: GEL
Manufacturer: Accupac LLC
Category: otc | Type: HUMAN OTC DRUG LABEL
Date: 20240918

ACTIVE INGREDIENTS: SODIUM FLUORIDE 0.243 g/100 g
INACTIVE INGREDIENTS: SODIUM LAUROYL SARCOSINATE; 1,2-HEXANEDIOL; FERROUS OXIDE; HYDRATED SILICA; LAURYL GLUCOSIDE; SUCRALOSE; SODIUM GLUCONATE; METHYL DIISOPROPYL PROPIONAMIDE; SODIUM PHOSPHATE; POTASSIUM PYROPHOSPHATE; ZINC LACTATE; XANTHAN GUM; XYLITOL; GLYCERIN; CARBOXYMETHYLCELLULOSE SODIUM, UNSPECIFIED FORM; WATER; SORBITOL

Active ingredient

Sodium Fluoride 0.243%

(0.14 w/v fluoride ion)

Purpose

Anticavity

Use

Aids in the prevention of dental cavities

Warnings

When using this product

Do not swallow

Do not use in eye area

Keep out of the reach of children under 6 years of age

If more than used for brushing is accidentally swallowed, get medical help of contact Poison Control Center right away.

Directions

Adults and children 2 years of age and older: Brush teeth thoroughly, preferably after each meal of at least twice a day, or use as directed by a dentist of doctor.

Instruct children under 6 years of age in good brushing and rinsing habits (to minimize swallowing).

Supervise children as necessary until capable of using without supervision.

Children under 2 years of age: Consult a dentist or doctor.

Inactive ingredients

Water, Sorbitol, Glycerin, Hydrated Silica, Xylitol, Sodium Phosphate, Xanthan Gum, Sodium Lauroyl Sarcosinate, Tetrapotassium Pyrophosphate, 1,2-Hexanediol, Cellulose Gum, Sucralose, Lauryl Glucoside, Methyl Diisopropyl Propionamide, Sodium Gluconate, Zinc Lactate, Iron Oxides